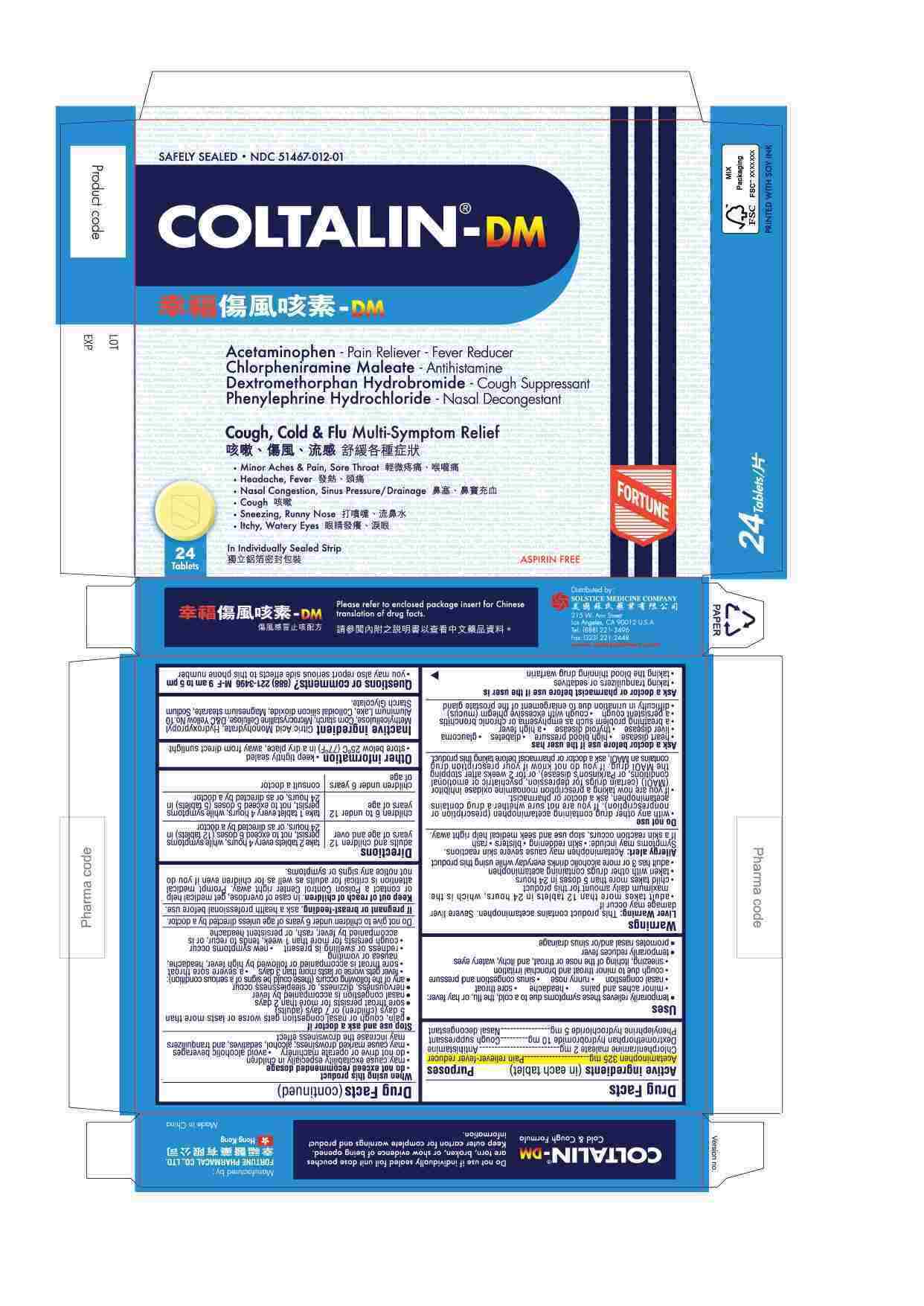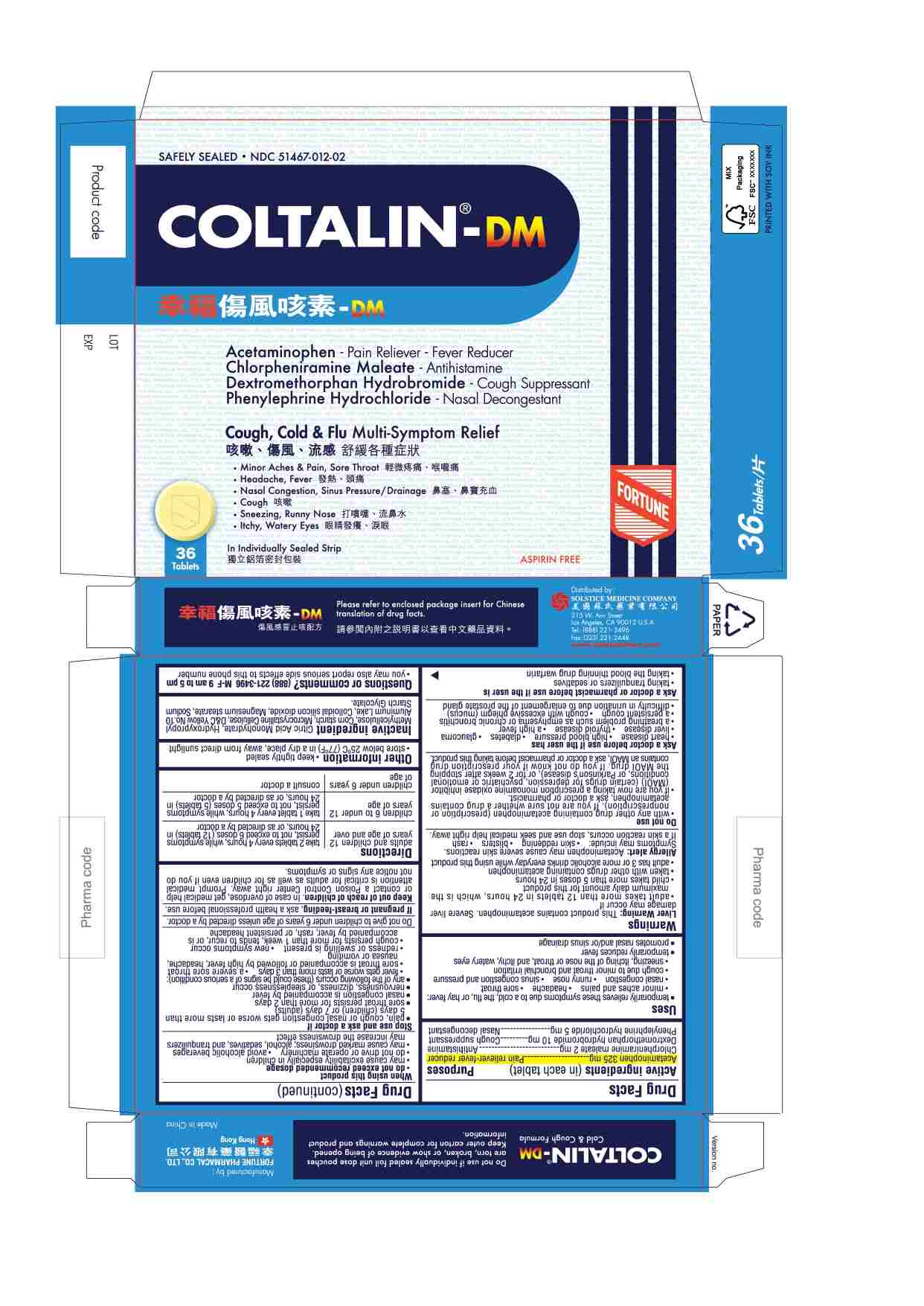 DRUG LABEL: COLTALIN-DM
NDC: 51467-007 | Form: TABLET
Manufacturer: FORTUNE PHARMACAL COMPANY LIMITED
Category: otc | Type: HUMAN OTC DRUG LABEL
Date: 20260213

ACTIVE INGREDIENTS: ACETAMINOPHEN 325 mg/1 1; CHLORPHENIRAMINE MALEATE 2 mg/1 1; DEXTROMETHORPHAN HYDROBROMIDE 10 mg/1 1; PHENYLEPHRINE HYDROCHLORIDE 5 mg/1 1
INACTIVE INGREDIENTS: MICROCRYSTALLINE CELLULOSE; CITRIC ACID MONOHYDRATE; HYDROXYPROPYL METHYLCELLULOSE; SILICON DIOXIDE; STARCH, CORN; D&C YELLOW NO. 10; MAGNESIUM STEARATE; SODIUM STARCH GLYCOLATE TYPE A POTATO

Drug Facts

Active ingredients (in each tablet)
Acetaminophen 325 mg
Chlorpheniramine maleate 2 mg
Dextromethorphan hydrobromide 10 mg
Phenylephrine hydrochloride 5 mg

Purposes
Pain reliever-fever reducer
Antihistamine
Cough suppressant
Nasal decongestant

Uses
■ temporarily relieves these symptoms due to a cold, the flu, or hay fever:
■ minor aches and pains
■ headache
■ sore throat
■ nasal congestion
■ runny nose
■ sinus congestion and pressure
■ cough due to minor throat and bronchial irritation
■ sneezing, itching of the nose or throat, and itchy, watery eyes due to hay fever
■ temporarily reduces fever
■ promotes nasal and/or sinus drainage

Warnings
Liver Warning:This product contains acetaminophen. Severe liver damage may occur if
■ adult takes more than 12 tablets in 24 hours, which is the maximum daily amount for this product
■ child takes more than 5 doses in 24 hours
■ taken with other drugs containing acetaminophen
■ adult has 3 or more alcoholic drinks everyday while using this product

Do not use
■ with any other drug containing acetaminophen (prescription or nonprescription). If you are not sure whether a drug contains acetaminophen, ask a doctor or pharmacist.
■ if the user is now taking a prescription monoamine oxidase inhibitor (MAOI) (certain drugs for depression, psychiatric or emotional conditions, or Parkinson's disease), or for 2 weeks after stopping the MAOI drug. If you do not know if your prescription drug contains an MAOI, ask a doctor or pharmacist before taking this product.

Ask a doctor before use if the user has
■ heart disease
■ high blood pressure
■ diabetes
■ glaucoma
■ liver disease
■ thyroid disease
■ a high fever
■ a breathing problem such as emphysema or chronic bronchitis
■ difficulty in urination due to enlargement of the prostate gland
■ a persistent cough

Ask a doctor or pharmacist before use if the user is
■ taking sedatives or tranquilizers
■ taking the blood thinning drug warfarin

When using this product
■ do not exceed recommended dosage
■ may cause excitability especially in children
■ do not drive or operate machinery
■ avoid alcoholic beverages
■ may cause marked drowsiness; alcohol, sedatives, and tranquilizers may increase the drowsiness effect

Stop use and ask a doctor if
■ pain or nasal congestion gets worse or lasts more than 5 days (children) or 7 days (adults)
■ sore throat persists for more than 2 days
■ nasal congestion is accompanied by fever
■ nervousness, dizziness, or sleeplessness occur
■ any of the following occurs (these could be signs of a serious condition):
■ fever gets worse or lasts more than 3 days
■ a severe sore throat
■ sore throat is accompanied or followed by fever, headache, rash, nausea or vomiting
■ redness or swelling is present
■ new symptoms occur
■ cough persists for more than 1 week, tends to recur, or is accompanied by fever rash, or persistent headache

Do not give to children under 6 years of age unless directed by a doctor.

PREGNANCY OR BREAST FEEDING

If pregnant or breast-feeding, ask a health professional before use.

Keep out of reach of children.In case of overdose, get medical help or contact a Poison Control Center right away. Prompt medical attention is critical for adults as well as for children even if you do not notice any signs or symptoms.

Directions
■ adults and children 12 years of age and over: 2 tablets every 4 hours, while symptoms persist, not to exceed 6 doses (12 tablets) in 24 hours, or as directed by a doctor
■ children 6 to under 12 years of age: 1 tablet every 4 hours, while symptoms persist, not to exceed 5 doses (5 tablets) in 24 hours, or as directed by a doctor
■ children under 6 of age : consult a doctor

Other information
■ keep tightly sealed
■ store between below 25 C (77 F) in a dry place, away from direct sunlight

Inactive ingredient

Citric Acid Monohydrate, Hydroxypropyl Methylcellulose, Corn starch, Microcrystalline Cellulose, D&C Yellow No.10 Aluminum Lake, Colloidal silicon dioxide, Magnesium stearate, Sodium Starch Glycolate.

Questions or comments?(888) 221-3496 M-F 9 am to 5 pm
■ you may also report serious side effects to this phone number

PACKAGE LABEL

COLTALIN-DM

Safely Sealed

NDC 51467-007-01

Acetaminophen - Pain Reliever-Fever Reducer
Chlorpheniramine Maleate - Antihistamine
Dextromethorphan Hydrobromide - Cough Suppressant
Phenylephrine Hydrochloride - Nasal Decongestant

Cough, Cold & Flu Multi-Symptom Relief
■ Minor Aches & Pain, Sore Throat
■ Headache, Fever
■ Nasal Congestion, Sinus Pressure/Drainage
■ Cough
■ Sneezing, Runny Nose
■ Itchy, Watery Eyes

24 Tablets

In Individually Sealed Strip

Aspirin Free

PACKAGE LABEL

COLTALIN-DM

Safely Sealed

NDC 51467-007-02

Acetaminophen - Pain Reliever-Fever Reducer
Chlorpheniramine Maleate - Antihistamine
Dextromethorphan Hydrobromide - Cough Suppressant
Phenylephrine Hydrochloride - Nasal Decongestant

Cough, Cold & Flu Multi-Symptom Relief
■ Minor Aches & Pain, Sore Throat
■ Headache, Fever
■ Nasal Congestion, Sinus Pressure/Drainage
■ Cough
■ Sneezing, Runny Nose
■ Itchy, Watery Eyes

36 Tablets

In Individually Sealed Strip

Aspirin Free